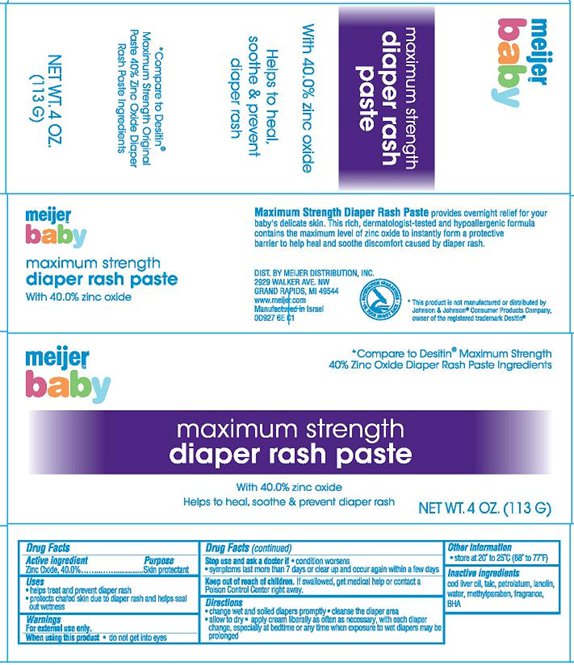 DRUG LABEL: Meijer Elements Maximum Strength For Diaper Rash
NDC: 41250-927 | Form: PASTE
Manufacturer: Meijer Distribution Inc.
Category: otc | Type: HUMAN OTC DRUG LABEL
Date: 20140114

ACTIVE INGREDIENTS: ZINC OXIDE 40 g/100 g
INACTIVE INGREDIENTS: COD LIVER OIL; TALC; PETROLATUM; LANOLIN; WATER; METHYLPARABEN; BUTYLATED HYDROXYANISOLE

Meijer Elements Maximum Strength For Diaper Rash Paste

Active ingredient

Zinc Oxide........40.0%

Purpose

Skin Protectant

Uses

- helps treat and prevent diaper rash
- protects chafed skin due to diaper rash and helps seal out wetness

Warnings

For external use only.

When using this product

- do not get into eyes

Stop use and ask a doctor if

- condition worsens
- symptoms last more than 7 days or clear up and occur again within a few days

Keep Out of Reach of Children.

If swallowed, get medical help or contact a Poison Control Center right away.

Directions

- change wet and soiled diapers promptly
- cleanse the diaper area
- allow to dry
- apply cream liberally as often as necessary, with each diaper change, especially at bedtime or any time when exposure to wet diapers may be prolonged

Other Information

- store at 20º to 25ºC (68º to 77ºF)

Inactive ingredients

cod liver oil, talc, petrolatum, lanolin, water, methylparaben, fragrance, BHA

Package/Label Principal Display Panel

meijer baby maximum strength diaper rash paste

With 40.0% zinc oxide

Helps to heal, soothe & prevent diaper rash

*Compare to Desitin®

Maximum Strength Original Paste 40% Zinc Oxide Diaper Rash Paste Ingredients

NET WT. 4 OZ. (113 G)

Quick Relief Diaper Rash Paste provides overnight relief for your baby's delicate skin. This rich, dermatologist-tested and hypoallergenic formula contains the maximum level of zinc oxide to instantly form a protective barrier to help heal and soothe discomfort caused by diaper rash.

DIST. BY MEIJER DISTRIBUTION, INC.
2929 WALKER AVE. NW
GRAND RAPIDS, MI 49544
www.meijer.com

Manufactured in Israel
0D927 6E C1

*This product is not manufactured or distributed by Johnson & Johnson® Consumer Products Company, owner of the registered trademark Desitin®

Carton Label